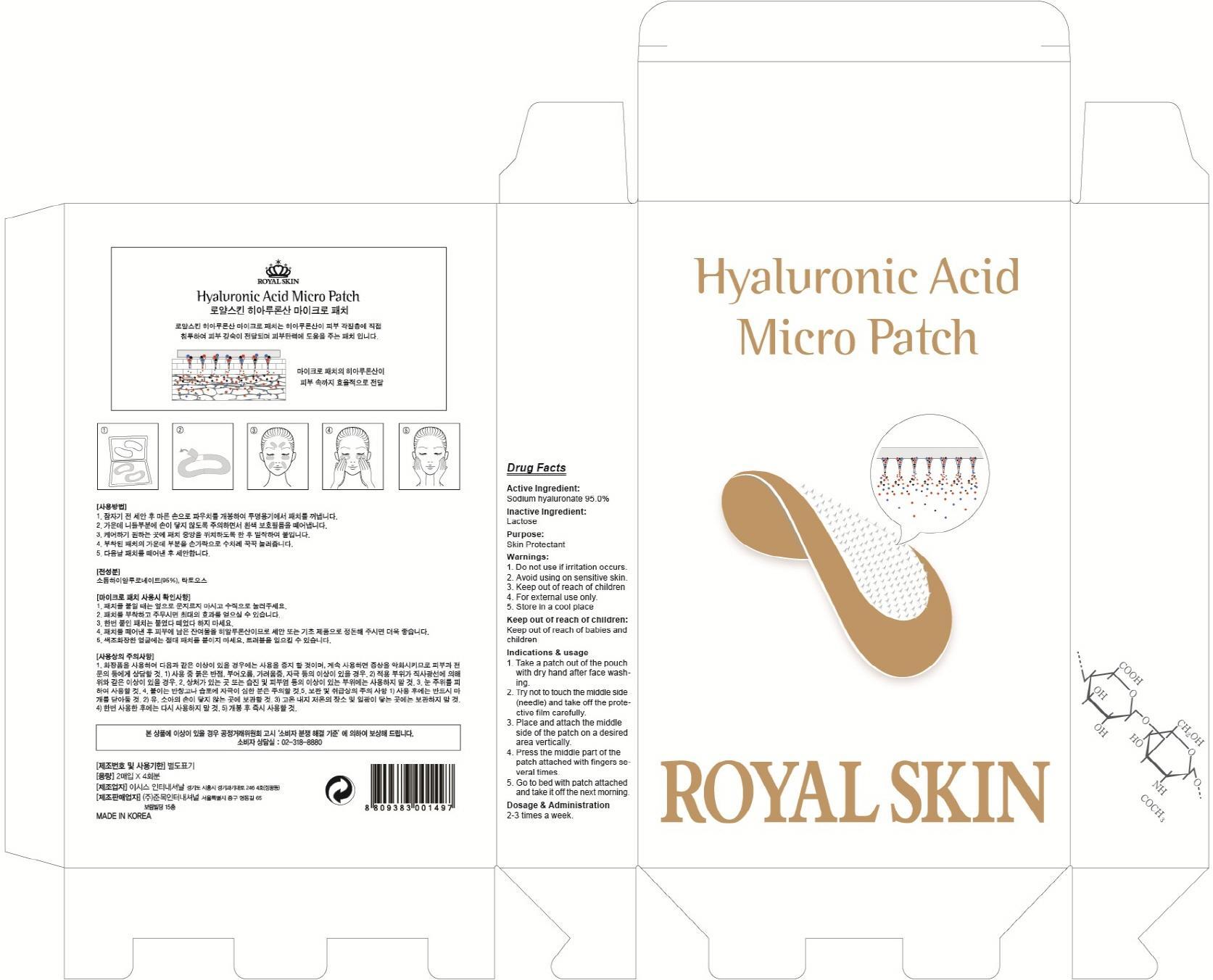 DRUG LABEL: Hyaluronic Acid Micro
NDC: 70018-010 | Form: PATCH
Manufacturer: JUNMOK INTERNATIONAL,INC
Category: otc | Type: HUMAN OTC DRUG LABEL
Date: 20150806

ACTIVE INGREDIENTS: HYALURONATE SODIUM 1.14 g/4 1
INACTIVE INGREDIENTS: Lactose

ACTIVE INGREDIENT

Active Ingredient: Sodium hyaluronate 95.0%

INACTIVE INGREDIENT

Inactive Ingredient: Lactose

PURPOSE

Purpose: Skin Protectant

WARNINGS

Warnings: 1. Do not use if irritation occurs. 2. Avoid using on sensitive skin. 3. Keep out of reach of children 4. For external use only. 5. Store in a cool place

KEEP OUT OF REACH OF CHILDREN

Keep out of reach of babies and children

INDICATIONS & USAGE

Indications & usage:1. Take a patch out of the pouch with dry hand after face washing. 2. Try not to touch the middle side (needle) and take off the protective film carefully. 3. Place and attach the middle side of the patch on a desired area vertically. 4. Press the middle part of the patch attached with fingers several times. 5. Go to bed with patch attached and take it off the next morning.

DOSAGE & ADMINISTRATION

Dosage & Administration: 2-3 times a week.